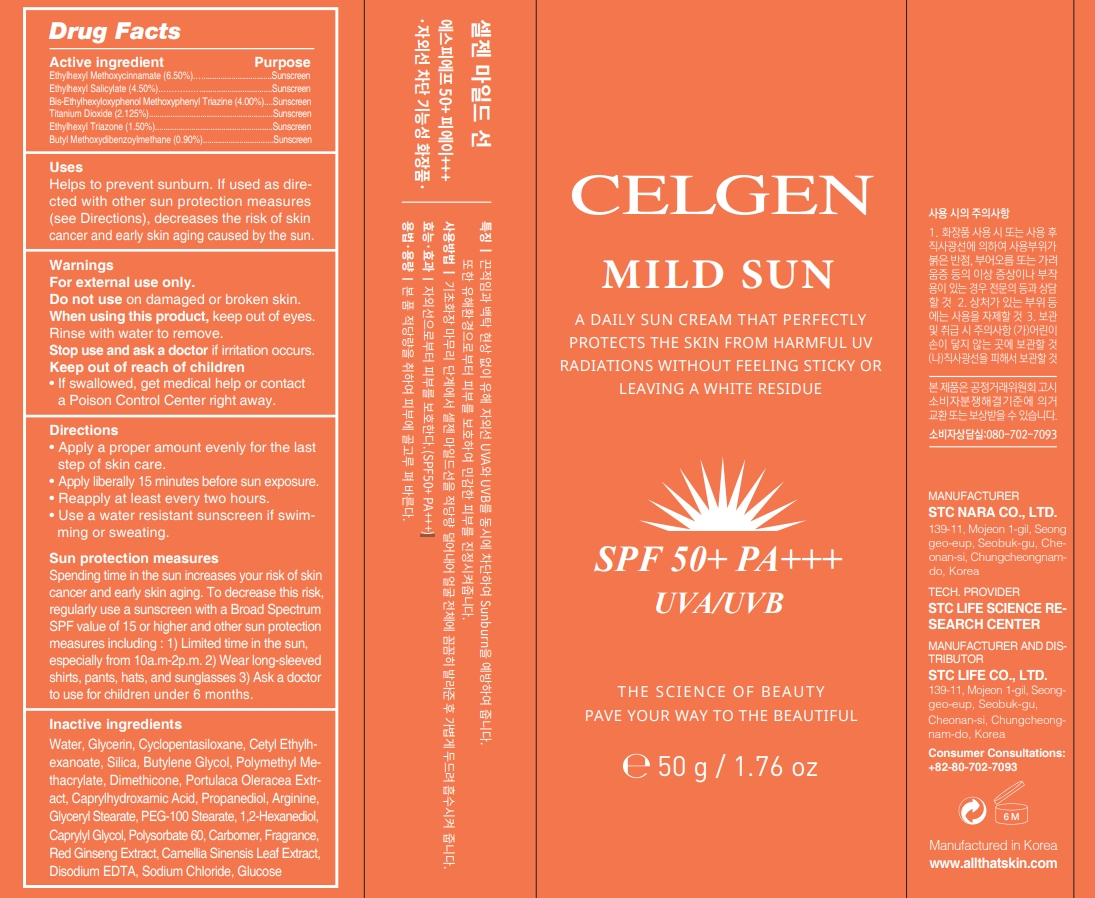 DRUG LABEL: CELGEN MILD SUN
NDC: 76731-204 | Form: CREAM
Manufacturer: BBHC CO., LTD
Category: otc | Type: HUMAN OTC DRUG LABEL
Date: 20200902

ACTIVE INGREDIENTS: TITANIUM DIOXIDE 2.125 g/100 g; ETHYLHEXYL TRIAZONE 1.5 g/100 g; AVOBENZONE 0.9 g/100 g; OCTINOXATE 6.5 g/100 g; OCTISALATE 4.5 g/100 g; BEMOTRIZINOL 4 g/100 g
INACTIVE INGREDIENTS: WATER; CYCLOMETHICONE 5; DIMETHICONE; CAPRYLHYDROXAMIC ACID; PROPANEDIOL; ARGININE; POLYSORBATE 60; GLYCERIN; CETYL ETHYLHEXANOATE; POLY(METHYL METHACRYLATE; 450000 MW); POLYOXYL 100 STEARATE; SILICON DIOXIDE; BUTYLENE GLYCOL; PURSLANE; GLYCERYL MONOSTEARATE; 1,2-HEXANEDIOL; CAPRYLYL GLYCOL; CARBOMER HOMOPOLYMER, UNSPECIFIED TYPE; ASIAN GINSENG; GREEN TEA LEAF; EDETATE DISODIUM ANHYDROUS; SODIUM CHLORIDE; ANHYDROUS DEXTROSE

76731-204

Active ingredient

Ethylhexyl Methoxycinnamate (6.50%)

Ethylhexyl Salicylate (4.50%)

Bis-Ethylhexyloxyphenol Methoxyphenyl Triazine (4.00%)

Titanium Dioxide (2.125%)

Ethylhexyl Triazone (1.50%)

Butyl Methoxydibenzoylmethane (0.90%)

Purpose

Sunscreen

Use

Helps to prevent sunburn. If used as directed with other sun protection measures (see Directions), decreases the risk of skin cancer and early skin aging caused by the sun.

Warnings

For external use only.

Do not use on damaged or broken skin.

When using this product, keep out of eyes. Rinse with water to remove.

Stop use and ask a doctor

if irritation occurs.

Keep out of reach of children

If swallowed, get medical help or contact a Poison Control Center right away.

Directions

• Apply a proper amount evenly for the last step of skin care.

• Apply liberally 15 minutes before sun exposure.

• Reapply at least every two hours.

• Use a water resistant sunscreen if swim- ming or sweating.

Sun protection measures.

Spending time in the sun increases your risk of skin cancer and early skin aging. To decrease this risk , regularly use a sunscreen with a Broad Spectrum SPF value of 15 or higher and other sun protection measures including : 1) Limited time in the sun, especially from 10a.m-2p.m. 2) Wear long-sleeved shirts, pants, hats, and sunglasses 3) Ask a doctor to use for children under 6 months.

Inactive ingredients

Water, Glycerin, Cyclopentasiloxane, Cetyl Ethylhexanoate, Silica, Butylene Glycol, Polymethyl Methacrylate, Dimethicone, Portulaca Oleracea Extract, Caprylhydroxamic Acid, Propanediol, Arginine, Glyceryl Stearate, PEG-100 Stearate, 1,2-Hexanediol, Caprylyl Glycol, Polysorbate 60, Carbomer, Fragrance, Red Ginseng Extract, Camellia Sinensis Leaf Extract, Disodium EDTA, Sodium Chloride, Glucose